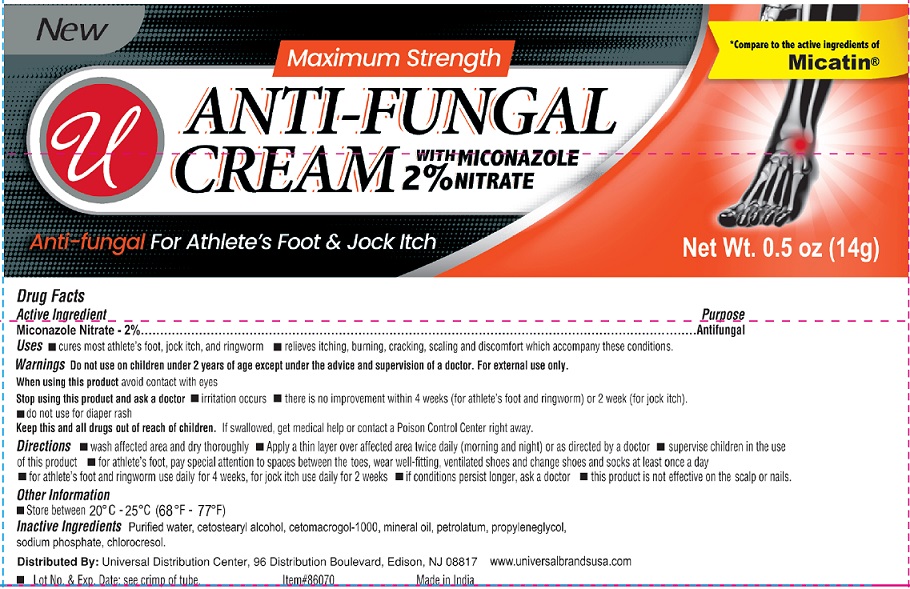 DRUG LABEL: Anti-Fungal
NDC: 52000-061 | Form: CREAM
Manufacturer: Universal Distribution Center LLC
Category: otc | Type: HUMAN OTC DRUG LABEL
Date: 20241203

ACTIVE INGREDIENTS: MICONAZOLE NITRATE 0.02 g/1 g
INACTIVE INGREDIENTS: WATER; CETOSTEARYL ALCOHOL; CETETH-20; MINERAL OIL; PETROLATUM; PROPYLENE GLYCOL; SODIUM PHOSPHATE; CHLOROCRESOL

Anti-Fungal Cream

Active Ingredient

Miconazole Nitrate 2%

Purpose

Antifungal

Uses

- cures most athlete's foot, jock itch, and ringworm.
- relieves itching, burning, cracking, scaling and discomfort which accompany these conditions.

Warnings

Do not use on children under 2 years of age except under the advice and supervision of a doctor.

For external use only.

When using this product avoid contact with eyes.

Stop using this product and ask a doctor

- irritation occurs
- there is no improvement within 4 weeks (for athlete’s foot and ringworm) or 2 weeks (for jock itch).
- do not use for diaper rash

KEEP OUT OF REACH OF CHILDREN

Keep this and all drugs out of reach of children.

If swallowed, get medical help or contact a Poison Control Center right away.

Directions

- wash affected area and dry thoroughly
- Apply a thin layer over affected area twice daily (morning and night) or as directed by a doctor
- supervise children in the use of this product
- for athlete's foot, pay special attention to spaces between the toes, wear well-fitting, ventilated shoes and change shoes and socks at least once a day
- for athlete's foot and ringworm use daily for 4 weeks, for jock itch use daily for 2 weeks
- if conditions persist longer, ask a doctor
- this product is not effective on the scalp or nails.

Other information

- Store between 20ºC to 25º C (68ºF to 77º F)
- Lot No. & Exp. Date: see crimp of tube.

Inactive Ingredients

Purified water, cetostearyl alcohol, cetomacrogol-1000, mineral oil, petrolatum, propyleneglycol, sodium phosphate, chlorocresol.

PACKAGE LABEL

PRINCIPAL DISPLAY PANEL

Anti-Fungal Cream

NET WT 0.5 OZ (14 g)